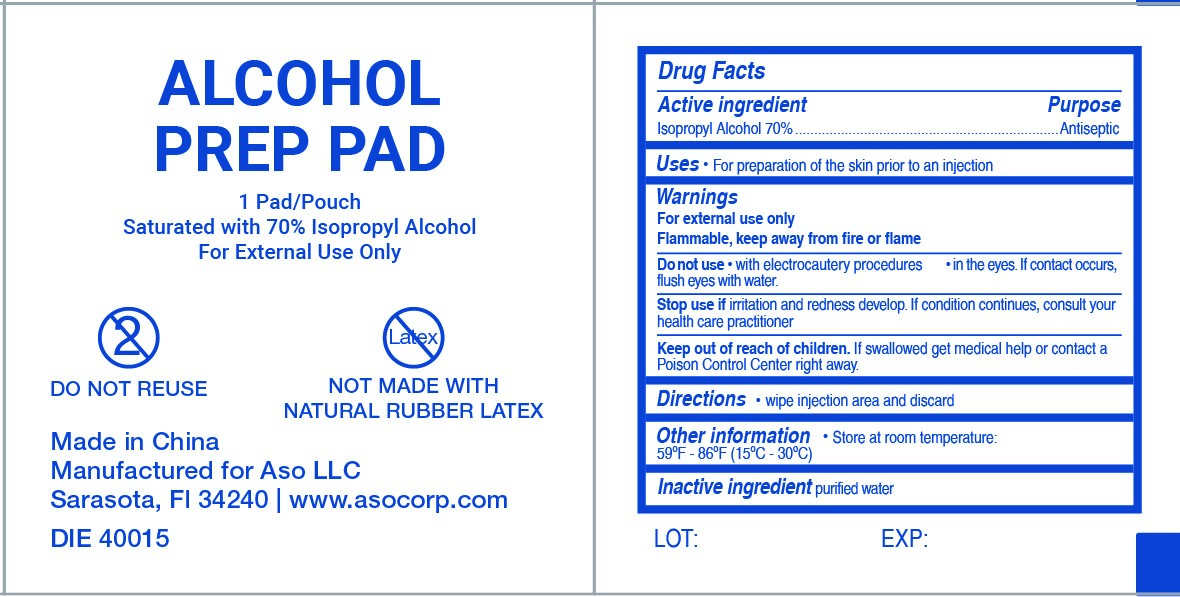 DRUG LABEL: Alcohol Prep Pad
NDC: 51142-444 | Form: LIQUID
Manufacturer: ASO LLC
Category: otc | Type: HUMAN OTC DRUG LABEL
Date: 20241101

ACTIVE INGREDIENTS: ISOPROPYL ALCOHOL 70 mL/100 mL
INACTIVE INGREDIENTS: WATER

Alcohol Prep Pad

Active Ingredient

Isopropyl Alcohol 70%

Purpose

Antiseptic

Uses

For preparation of the skin prior to an injection.

Warnings

For external use only

Flammable, keep away from fire or flame

Do not use

- with electrocautery procedures
- in the eyes. If contact occurs, flush eyes with water.

Stop use if

irritation and redness develop. If condition continues, consult you health care practitioner.

Keep out of reach of children

If swallowed get medical help or contact a Poison Control Center right away.

Directions

wipe ingection area and discard

Other Information

Store at room temperature: 59ºF - 86ºF (15ºC - 30ºC)

Inactice ingredient

purified water

Principal DIsplay Panel

ALCOHOL PREP PAD

1 Pad/Pouch

Saturated with 70% Isopropyl Alcohol

For External Use Only

DO NOT REUSE

NOT MADE WITH NATURAL RUBBER LATEX